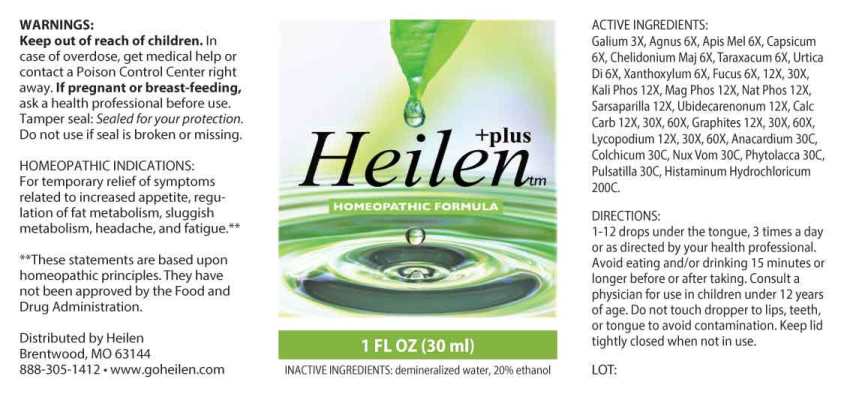 DRUG LABEL: Heilen
NDC: 70719-0003 | Form: LIQUID
Manufacturer: Heilen
Category: homeopathic | Type: HUMAN OTC DRUG LABEL
Date: 20260112

ACTIVE INGREDIENTS: GALIUM APARINE WHOLE 3 [hp_X]/1 mL; CHASTE TREE FRUIT 6 [hp_X]/1 mL; APIS MELLIFERA 6 [hp_X]/1 mL; CAPSICUM 6 [hp_X]/1 mL; CHELIDONIUM MAJUS WHOLE 6 [hp_X]/1 mL; TARAXACUM OFFICINALE 6 [hp_X]/1 mL; URTICA DIOICA WHOLE 6 [hp_X]/1 mL; ZANTHOXYLUM AMERICANUM BARK 6 [hp_X]/1 mL; FUCUS VESICULOSUS 6 [hp_X]/1 mL; DIBASIC POTASSIUM PHOSPHATE 12 [hp_X]/1 mL; MAGNESIUM PHOSPHATE, DIBASIC TRIHYDRATE 12 [hp_X]/1 mL; SODIUM PHOSPHATE, DIBASIC, HEPTAHYDRATE 12 [hp_X]/1 mL; SMILAX ORNATA ROOT 12 [hp_X]/1 mL; UBIDECARENONE 12 [hp_X]/1 mL; OYSTER SHELL CALCIUM CARBONATE, CRUDE 12 [hp_X]/1 mL; GRAPHITE 12 [hp_X]/1 mL; LYCOPODIUM CLAVATUM SPORE 12 [hp_X]/1 mL; SEMECARPUS ANACARDIUM JUICE 30 [hp_C]/1 mL; COLCHICUM AUTUMNALE BULB 30 [hp_C]/1 mL; STRYCHNOS NUX-VOMICA SEED 30 [hp_C]/1 mL; PHYTOLACCA AMERICANA ROOT 30 [hp_C]/1 mL; PULSATILLA PRATENSIS WHOLE 30 [hp_C]/1 mL; HISTAMINE DIHYDROCHLORIDE 200 [hp_C]/1 mL
INACTIVE INGREDIENTS: WATER; ALCOHOL

DRUG FACTS:

ACTIVE INGREDIENTS:

Galium Aparine 3X, Agnus Castus 6X, Apis Mellifica 6X, Capsicum Annuum 6X, Chelidonium Majus 6X, Taraxacum Officinale 6X, Urtica Dioica 6X, Xanthoxylum Fraxineum 6X, Fucus Vesiculosus 6X, 12X, 30X, Kali Phosphoricum 12X, Magnesia Phosphorica 12X, Natrum Phosphoricum12X, Sarsaparilla (Smilax Regelii) 12X, Ubidecarenonum 12X, Calcarea Carbonica 12X, 30X, 60X, Graphites 12X, 30X, 60X, Lycopodium Clavatum 12X, 30X, 60X, Anacardium Orientale 30C, Colchicum Autumnale 30C, Nux Vomica 30C, Phytolacca Decandra 30C, Pulsatilla (Pratensis) 30C, Histaminum Hydrochloricum 200C.

HOMEOPATHIC INDICATIONS:

For temporary relief of symptoms related to increased appetite, regulation of fat metabolism, sluggish metabolism, headache, and fatigue.**

**These statements are based upon homeopathic principles. They have not been approved by the Food and Drug Administration.

WARNINGS:

Keep out of reach of children. In case of overdose, get medical help or contact a Poison Control Center right away.

If pregnant or breast-feeding, ask a health professional before use.

Tamper seal: Sealed for Your Protection. Do not use if seal is broken or missing.

Keep out of reach of children. In case of overdose, get medical help or contact a Poison Control Center right away.

DIRECTIONS:

1-12 drops under the tongue, 3 times a day or as directed by your health professional. Avoid eating and/or drinking 15 minutes or longer before or after taking. Consult a physician for use in children under 12 years of age. Do not touch dropper to lips, teeth, or tongue to avoid contamination. Keep lid tightly closed when not in use.

HOMEOPATHIC INDICATIONS:

For temporary relief of symptoms related to increased appetite, regulation of fat metabolism, sluggish metabolism, headache, and fatigue.**

**These statements are based upon homeopathic principles. They have not been approved by the Food and Drug Administration.

INACTIVE INGREDIENTS:

demineralized water, 20% ethanol

QUESTIONS:

Distributed by Heilen

Brentwood, MO 63144

888-305-1412 • www.goheilen.com

PACKAGE LABEL DISPLAY:

+plus

Heilen

HOMEOPATHIC FORMULA

1 FL OZ (30 ml)